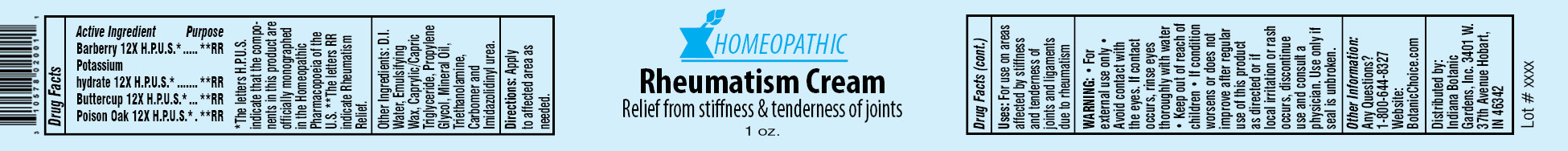 DRUG LABEL: Homeopathic Rheumatism
NDC: 10578-020 | Form: CREAM
Manufacturer: Indiana Botanic Gardens
Category: homeopathic | Type: HUMAN OTC DRUG LABEL
Date: 20120427

ACTIVE INGREDIENTS: BERBERIS VULGARIS ROOT BARK 12 [hp_X]/28 g; CAUSTICUM 12 [hp_X]/28 g; RANUNCULUS BULBOSUS 12 [hp_X]/28 g; TOXICODENDRON PUBESCENS LEAF 12 [hp_X]/28 g
INACTIVE INGREDIENTS: WATER; CETOSTEARYL ALCOHOL; POLYSORBATE 60; TRICAPRYLIN; PROPYLENE GLYCOL; MINERAL OIL; TROLAMINE; CARBOMER 934; IMIDUREA

Homeopathic Rheumatism Cream

Active Ingredients

Barberry 12X H.P.U.S.*

Potassium hydrate 12X H.P.U.S.*

Buttercup 12X H.P.U.S.*

Poison Oak 12X H.P.U.S.*

Purpose

**RR

**RR

**RR

**RR

*The letters H.P.U.S. indicate that the components in this product are officially monographed in the Homeopathic Pharmacopoeia of the U.S. **The letters RR indicate Rheumatism Relief.

Other Ingredients:

D.I. Water, Emulsifying Wax, Caprylic/Capric Triglyceride, Propylene Glycol, Mineral Oil, Triethanolamine, Carbomer and Imidazolidinyl urea.

Directions:

Apply to affected area as needed.

Uses:

For use on areas affected by stiffness and tenderness of joints and ligaments due to rheumatism

WARNING:

- for external use only
- Avoid contact with the eyes. If contact occurs, rinse eyes thoroughly with water

- Keep out of reach of children

STOP USE

- If condition worsens or does not improve after regular use of this product as directed or if local irritation or rash occurs, discontinue use and consult a physician.

Use only if seal is unbroken.

Other Information:

Any Questions?

1-800-644-8327

Website:

BotanicChoice.com

Distributed by:

Indiana Botanic Gardens, Inc. 3401 W. 37th Avenue Hobart, IN 46342

Homeopathic Rheumatism Cream

Relief from stiffness & tenderness of joints

1 oz.